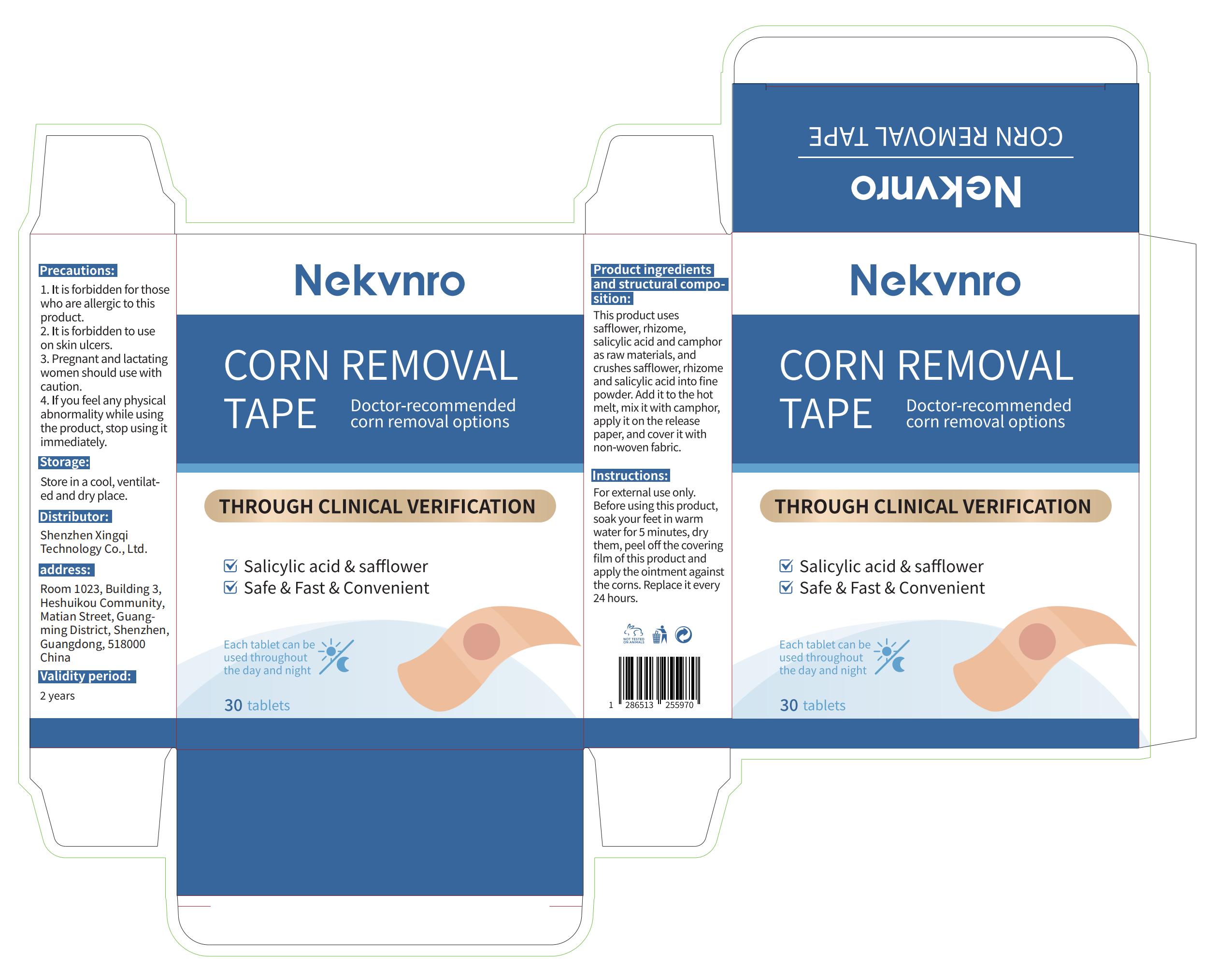 DRUG LABEL: Nekvnro Corn Removal Tape
NDC: 84613-053 | Form: PATCH
Manufacturer: Shenzhen Xingqi Technology Co., Ltd.
Category: otc | Type: HUMAN OTC DRUG LABEL
Date: 20240809

ACTIVE INGREDIENTS: SALICYLIC ACID 1 g/100 g; SAFFLOWER 1 g/100 g
INACTIVE INGREDIENTS: ANGELICA DAHURICA ROOT; CAMPHORIC ACID

ACTIVE INGREDIENT

SAFFLOWER 1%

SALICYLIC ACID 5%

Purpose

CORN REMOVAL

uses

For external use only. Before using this product, soak your feet in warm water for 5 minutes, dry them, peel off the covering film of this product and apply the ointment against the corns. Replace it every 24 hours.

warning

1. It is forbidden for those who are allergic to this product.
2. It is forbidden to use on skin ulcers.
3. Pregnantand lactating women should use with caution.
4. If you feel any physical abnormality while using the product, stop using it immediately.

DOSAGE ADMINISTRATION

For external use only.

DO NOT USE

1. It is forbidden for those who are allergic to this product.
2. It is forbidden to use on skin ulcers.
3. Pregnantand lactating women should use with caution.
4. If you feel any physical abnormality while using the product, stop using it immediately.

When using section

If you feel any physical abnormality while using the product, stop using it immediately.

STOP USE

It is forbidden to use on skin ulcers.

Keep out of reach of children.

Keep Away From Children Under 3 Years Old And Pets,Out Of Direct Sunlight And Store In A Cool, Dry Place

Inactive ingredients

ANGELICA DAHURICA ROOT , CAMPHORIC ACID